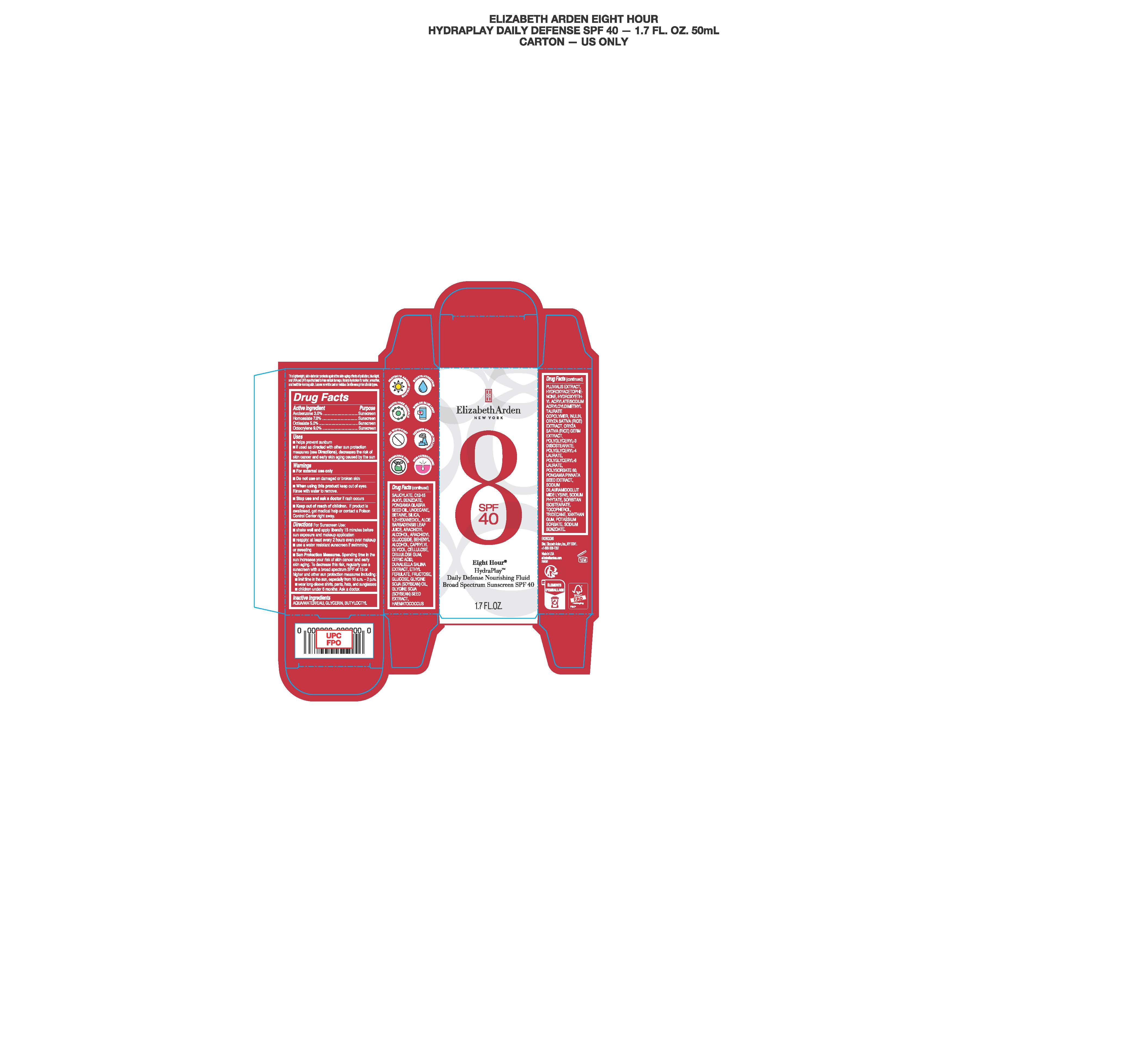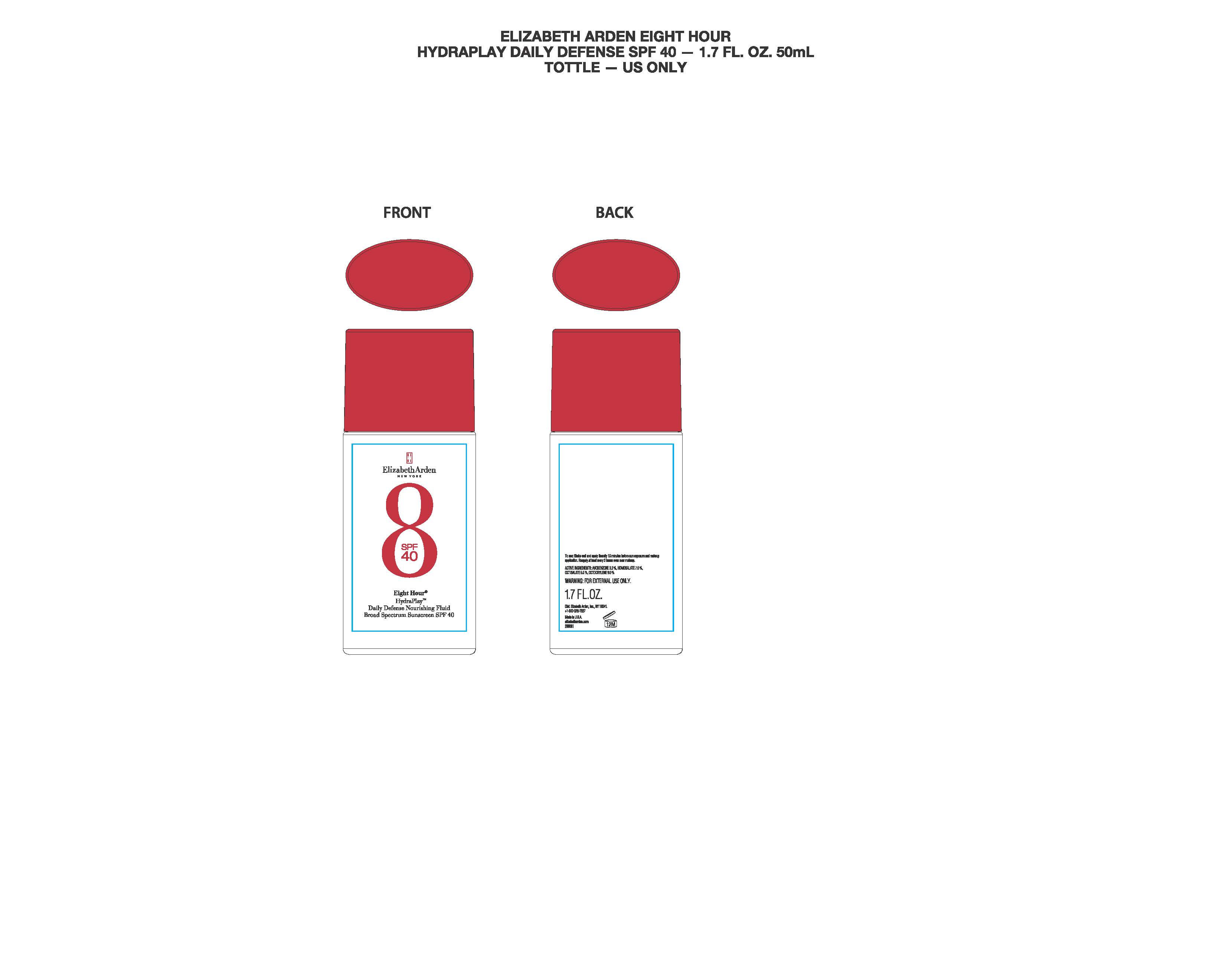 DRUG LABEL: Elizabeth Arden Eight Hour Hydraplay SPF 40
NDC: 10967-788 | Form: CREAM
Manufacturer: Revlon Consumer Products Corp
Category: otc | Type: HUMAN OTC DRUG LABEL
Date: 20250616

ACTIVE INGREDIENTS: HOMOSALATE 3.5 g/50 g; OCTOCRYLENE 4.5 g/50 g; OCTISALATE 2.5 g/50 g; AVOBENZONE 1.5 g/50 g
INACTIVE INGREDIENTS: SODIUM DILAURAMIDOGLUTAMIDE LYSINE; SORBITAN ISOSTEARATE; POTASSIUM SORBATE; WATER; ALOE VERA LEAF; FRUCTOSE; HYDROXYETHYL ACRYLATE/SODIUM ACRYLOYLDIMETHYL TAURATE COPOLYMER (45000 MPA.S AT 1%); SODIUM PHYTATE; SODIUM BENZOATE; GLYCERIN; PONGAMIA GLABRA SEED OIL; ARACHIDYL ALCOHOL; BETAINE; BUTYLOCTYL SALICYLATE; C12-15 ALKYL BENZOATE; UNDECANE; 1,2-HEXANEDIOL; CITRIC ACID; TOCOPHEROL; ARACHIDYL GLUCOSIDE; POWDERED CELLULOSE; DUNALIELLA SALINA; PONGAMIA PINNATA SEED; INULIN; POLYSORBATE 60; CAPRYLYL GLYCOL; GLUCOSE; SOYBEAN OIL; HAEMATOCOCCUS PLUVIALIS; POLYGLYCERYL-4 LAURATE; SILICA; CELLULOSE GUM; ETHYL FERULATE; HYDROXYACETOPHENONE; RICE GERM; POLYGLYCERYL-3 DIISOSTEARATE; POLYGLYCERYL-6 LAURATE; TRIDECANE; XANTHAN GUM; GLYCINE SOJA (SOYBEAN) SEED; BEHENYL ALCOHOL

Elizabeth Arden Eight Hour Hydraplay SPF 40

Active Ingredients

Avobenzone 3.0 %

Homosalate 7.0 %

Octisalate 5.0 %

Octocrylene 9.0 %

Uses

- helps prevent sunburn
- if used as directed with other sun protection measures (see Directions), decreases the risk of skin cancer and early skin aging caused by the sun

Purpose

Sunscreen

Warnings

- Stop use and ask doctor if rash occurs

Warnings

Do not use on damaged or broken skin

Warnings

When using this product keep out of eyes. Rinse with water to remove.

Warnings

Keep out of reach of children. If product is swallowed, get medical help or contact a Poison Control Center right away.

Warnings

For external use only.

Inactive Ingredients

Aqua/Water/Eau, Glycerin, Butyloctyl Salicylate, C12-15 Alkyl Benzoate, Pongamia Glabra Seed Oil, Undecane, Betaine, Silica, 1,2-Hexanediol, Aloe Barbadensis Leaf Juice, Arachidyl Alcohol, Arachidyl Glucoside, Behenyl Alcohol, Caprylyl Glycol, Cellulose, Cellulose Gum, Citric Acid, Dunaliella Salina Extract, Ethyl Ferulate, Fructose, Glucose, Glycine Soja (Soybean) Oil, Glycine Soja (Soybean) Seed Extract, Haematococcus Pluvialis Extract, Hydroxyacetophenone, Hydroxyethyl Acrylate/Sodium Acryloyldimethyl Taurate Copolymer, Inulin, Oryza Sativa (Rice) Extract, Oryza Sativa (Rice) Germ Extract, Polyglyceryl-3 Diisostearate, Polyglyceryl-4 Laurate, Polyglyceryl-6 Laurate, Polysorbate 60, Pongamia Pinnata Seed Extract, Sodium Dilauramidoglutamide Lysine, Sodium Phytate, Sorbitan Isostearate, Tocopherol, Tridecane, Xanthan Gum, Potassium Sorbate, Sodium Benzoate.

Directions

Directions For Sunscreen Use:

- shake well and apply liberally 15 minutes before sun exposure and makeup application
- reapply: at least every 2 hours even over makeup
- use a water resistant sunscreen if swimming or sweating
- Sun Protection Measures. Spending timine in the sun increases your risk of skin cancer and early skin aging. To decrease this risk, regularly use a sunscreen with broad spectrum SPF of 15 or higher and other sun protection measures including:
- limit time in the sun, especially from 10 a.m. - 2 p.m.
- wear long-sleeve shirts, pants, hats, and sunglasses
- children under 6 months: Ask a doctor.

Directions For Sunscreen Use

- Shake well and apply liberally 15 minutes before sun exposure and makeup application
- Reapply: at least every 2 hours even over makeup
- use a water resistant sunscreen if swimming or sweating